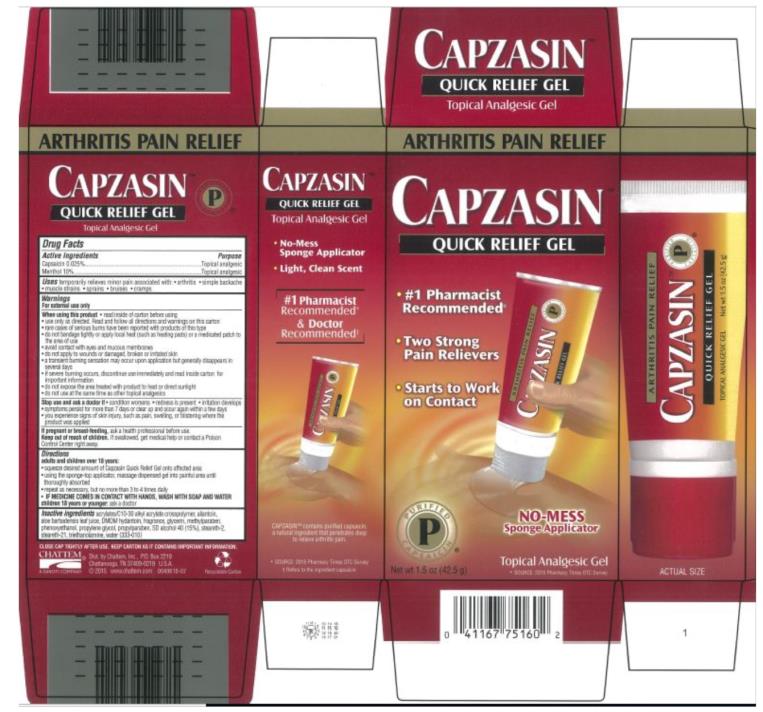 DRUG LABEL: Capzasin Quick Relief
NDC: 41167-7516 | Form: GEL
Manufacturer: Chattem, Inc.
Category: otc | Type: HUMAN OTC DRUG LABEL
Date: 20231025

ACTIVE INGREDIENTS: CAPSAICIN 0.00025 g/1 g; MENTHOL 0.1 g/1 g
INACTIVE INGREDIENTS: ALLANTOIN; ALOE VERA LEAF; GLYCERIN; METHYLPARABEN; PHENOXYETHANOL; PROPYLENE GLYCOL; PROPYLPARABEN; TROLAMINE; WATER; CARBOMER INTERPOLYMER TYPE A (55000 CPS); STEARETH-2; STEARETH-21

Capzasin Quick Relief

Capzasin Quick Relief Gel

Active Ingredient

Capsaicin 0.025%

Purpose

Topical analgesic

Active Ingredient

Menthol 10%

Purpose

Topical analgesic

Uses

temporarily relieves minor pain associated with:

- arthritis
- simple backache
- muscle strains
- sprains
- bruises
- cramps

Warnings

For external use only

When using this product

- read inside of carton before using
- use only as directed. Read and follow all directions and warnings on this carton/label.
- avoid contact with the eyes and mucous membranes
- rare cases of serious burns have been reported with products of this type
- do not bandage tightly or apply local heat (such as heating pads) or a medicated patch to the area of use
- do not apply to wounds or damaged, broken or irritated skin
- do not use at the same time as other topical analgesics
- a transient burning sensation may occur upon application but generally disappears in several days
- if severe burning occurs, discontinue use immediately and read inside carton for important information
- do not expose the area treated with product to heat or direct sunlight
- avoid applying into skin folds

Stop use and ask a doctor if

- condition worsens
- redness is present
- irritation develops
- symptoms persist for more than 7 days or clear up and occur again within a few days
- you experience signs of skin injury, such as pain, swelling, or blistering where the product was applied

If pregnant or breast-feeding

ask a health professional before use.

Keep out of reach of children.

If swallowed, get medical help or contact a Poison Control Center right away.

Directions

adults and children over 18 years:

- squeeze desired amount of Capzasin Quick Relief Gel onto affected area
- using the sponge-top applicator, massage dispensed gel into painful area until thoroughly absorbed
- repeat as necessary, but no more than 3 to 4 times daily
- IF MEDICINE COMES IN CONTACT WITH HANDS, WASH WITH SOAP AND WATER

children 18 years or younger: ask a doctor

Inactive Ingredients

acrylates/C10-30 alkyl acrylate crosspolymer, allantoin, aloe barbadensis leaf juice, DMDM hydantoin, fragrance, glycerin, methylparaben, phenoxyethanol, propylene glycol, propylparaben, SD alcohol 40-2 (15%), steareth-2, steareth-21, triethanolamine, water (245-285)
KEEP CARTON AS IT CONTAINS IMPORTANT INFORMATION.

Distributed by: Chattem, Inc.
P.O. Box 2219
Chattanooga, TN 37409-0219
0049618-03 U.S.A. ©2010 www.chattem.com Recyclable Carton

Principal Display Panel

ARTHRITIS PAIN RELIEF
CAPZASIN TM
QUICK RELIEF GEL

- #1 Pharmacist
  Recommended*
- Two Strong
  Pain Relievers
- Starts to Work
  on Contact

NO-MESS
Sponge Applicator
PURIFIED
P
CAPSAICIN®
Topical Analgesic Gel
*SOURCE: 2009 Pharmacy Today Survey
Net wt 1.5 oz (42.5 g)